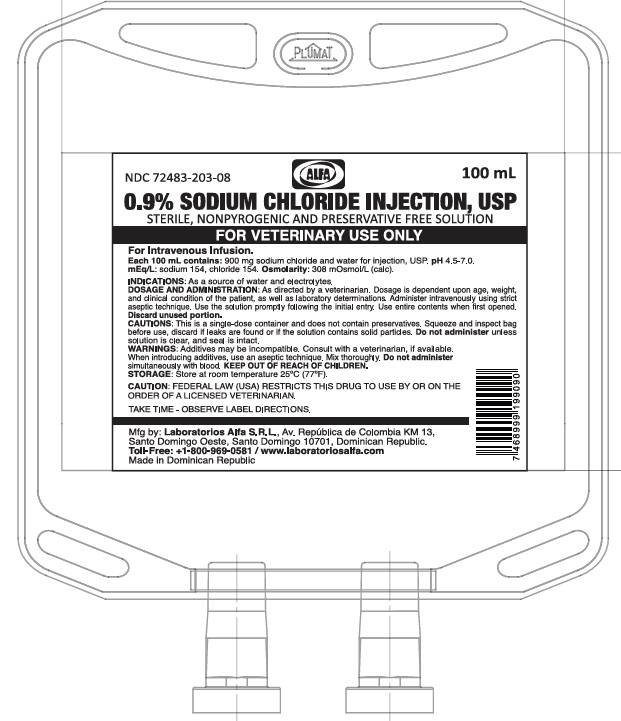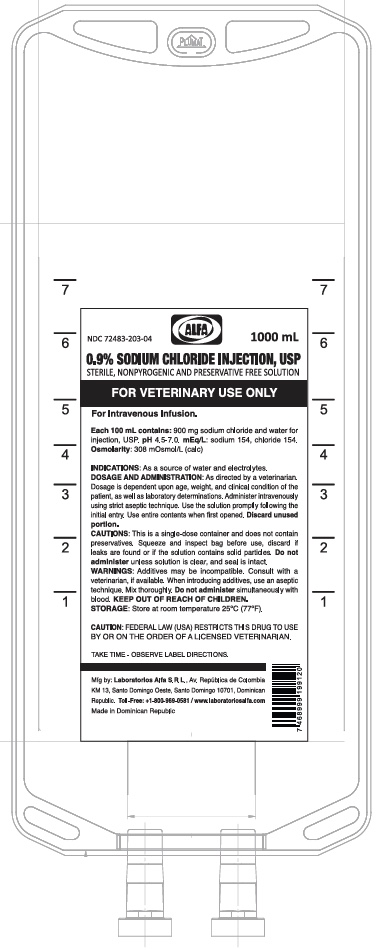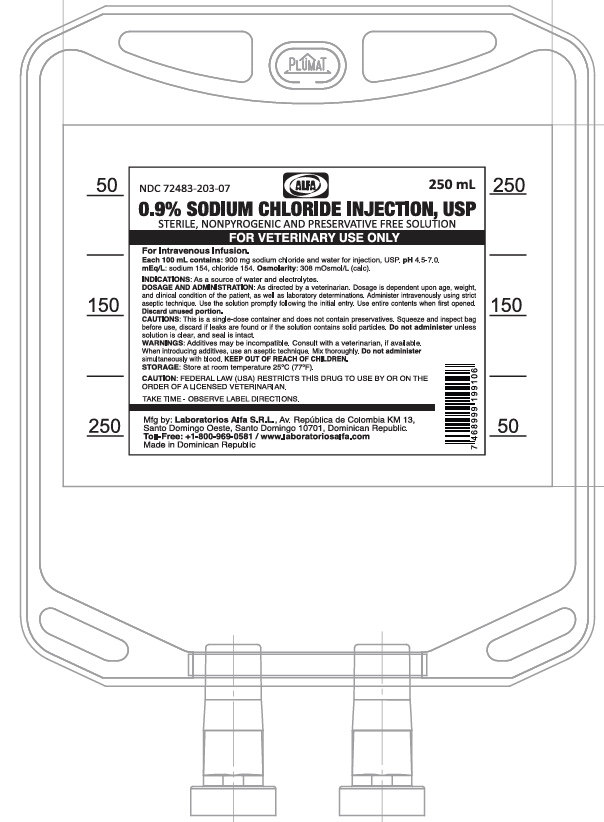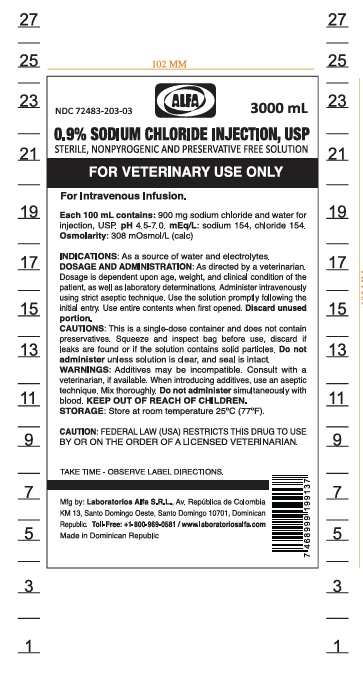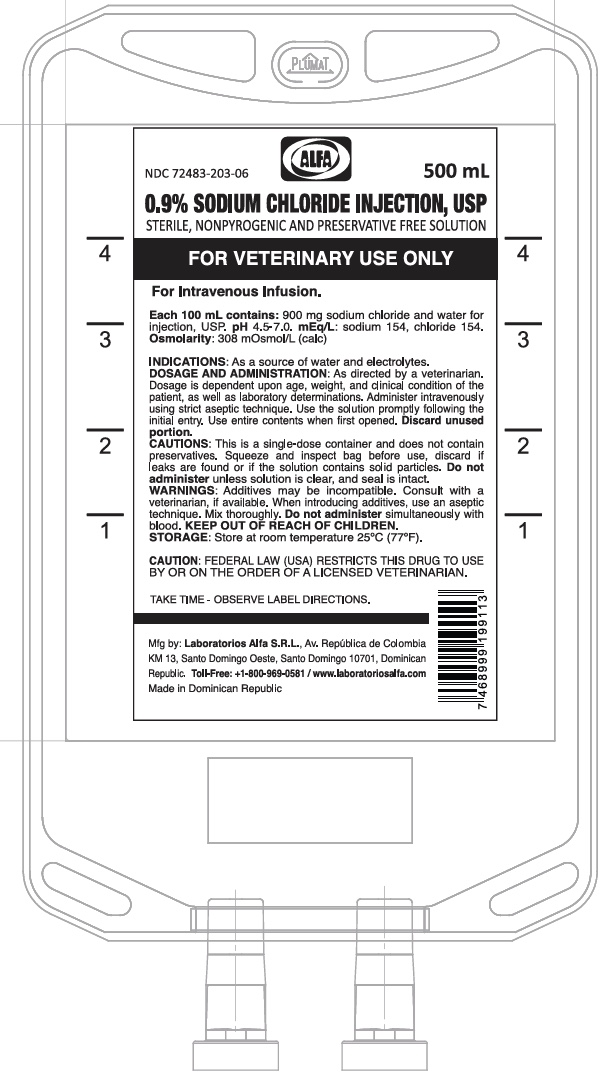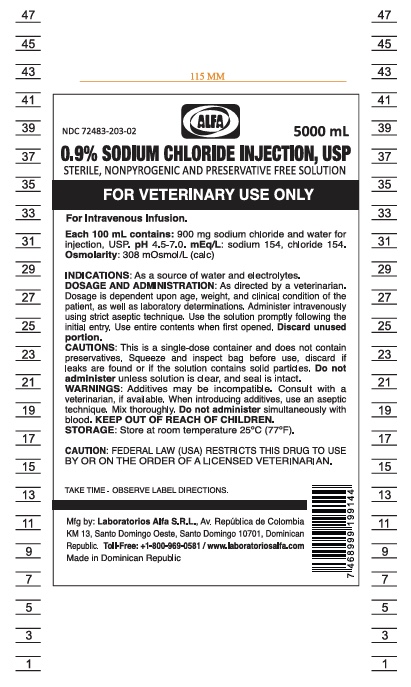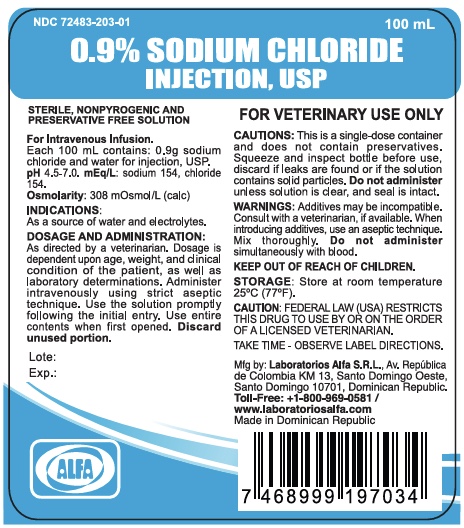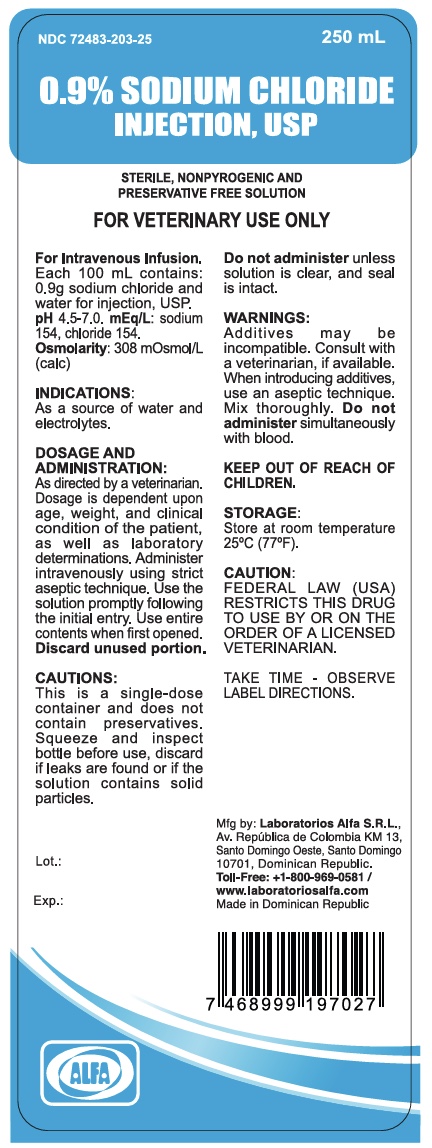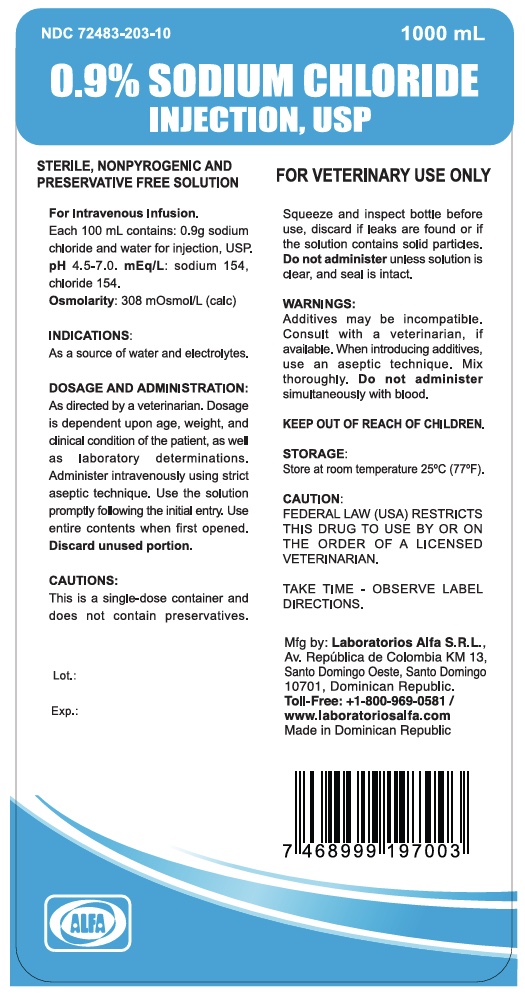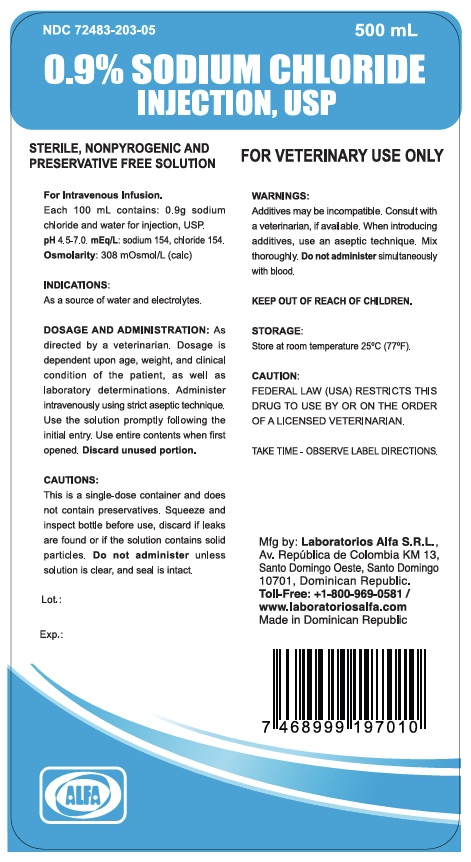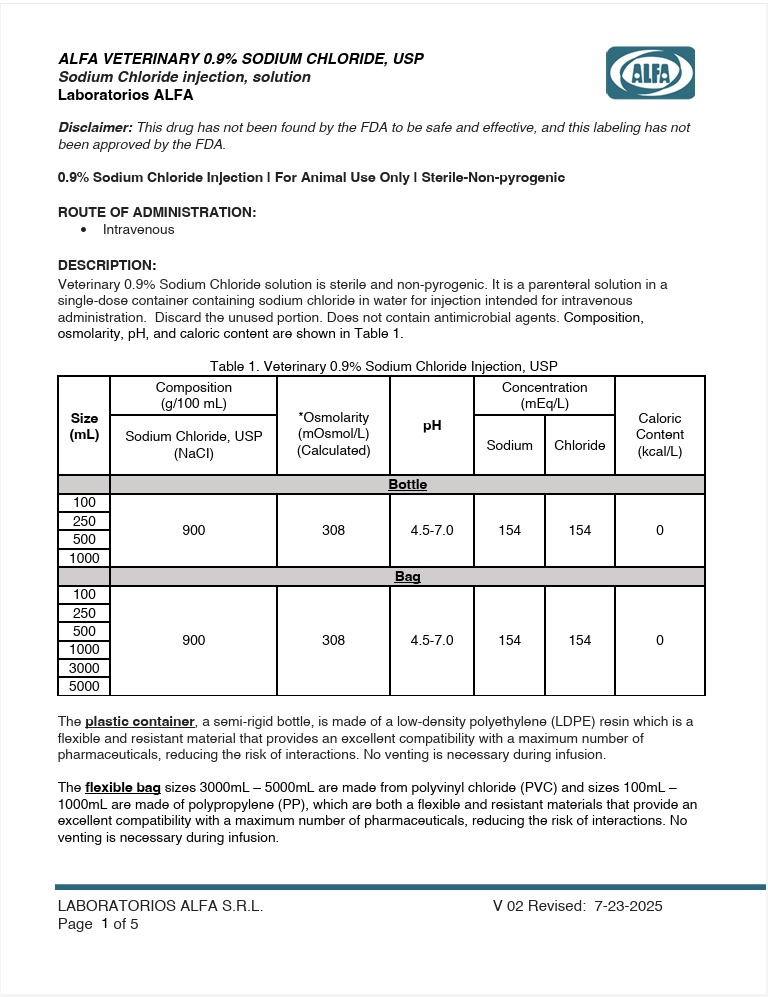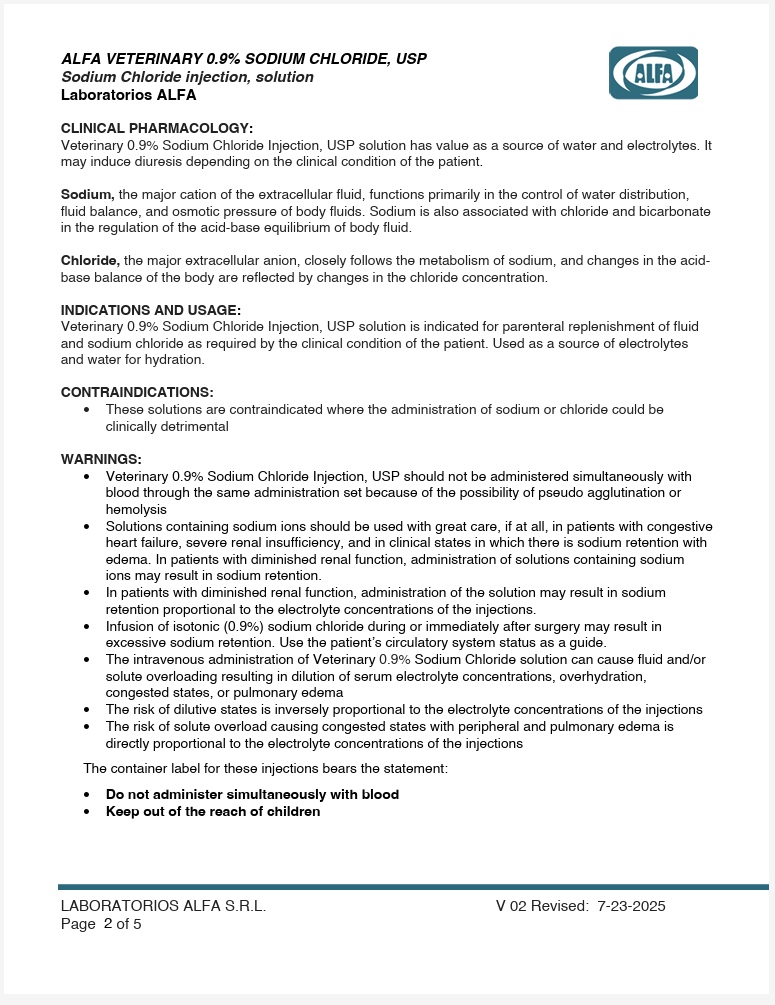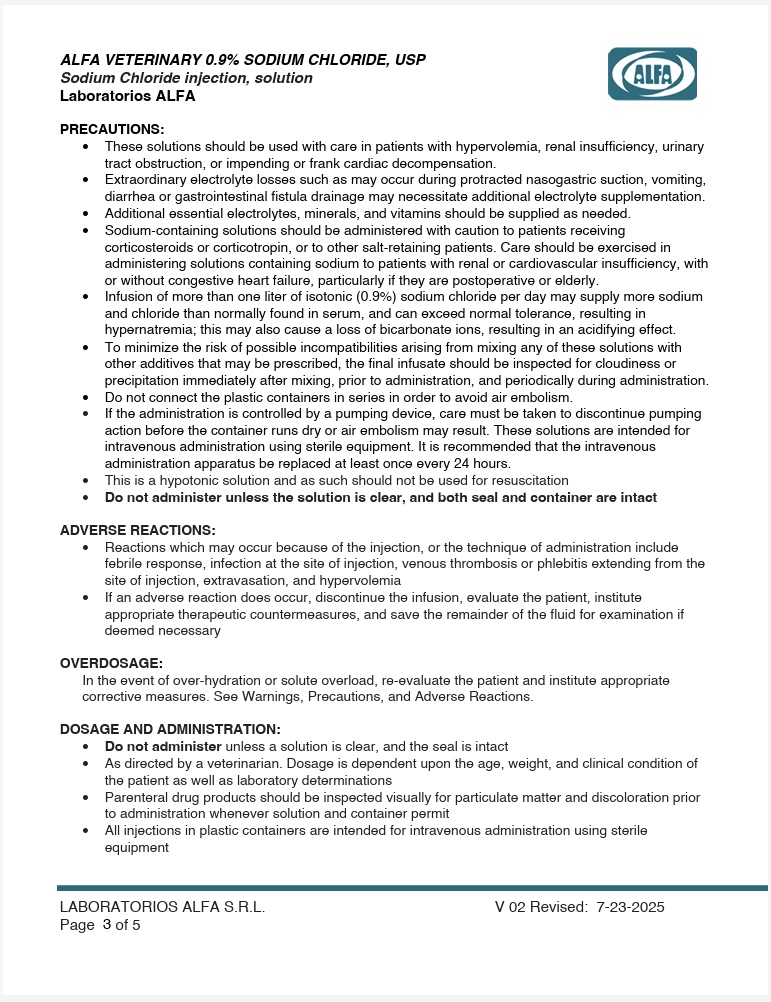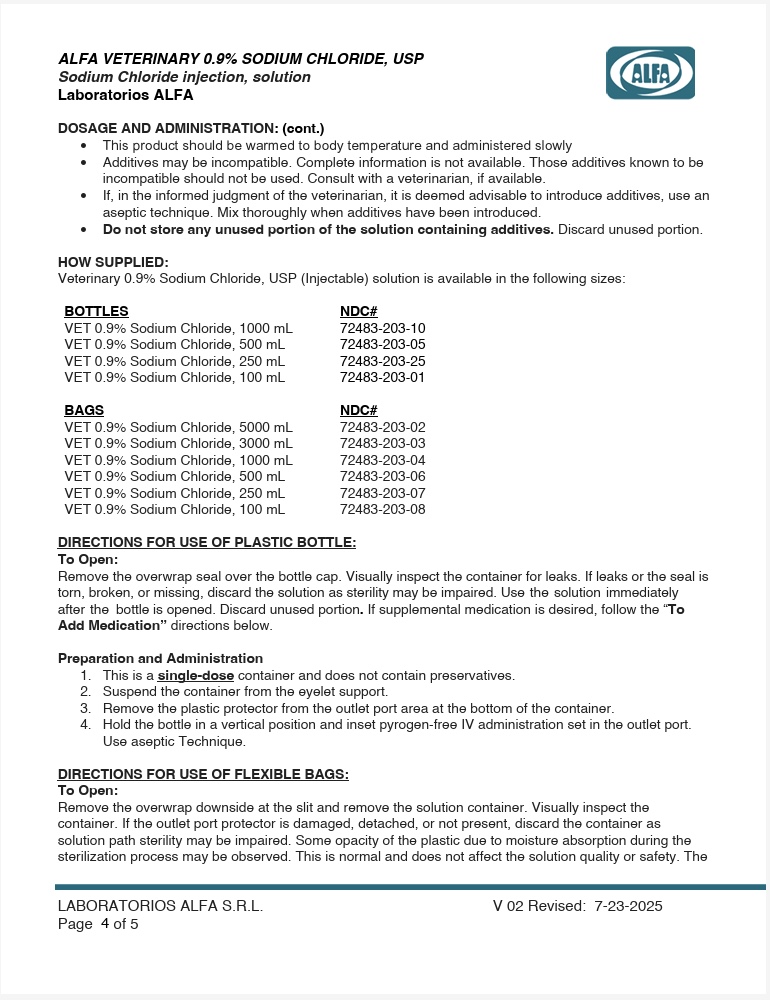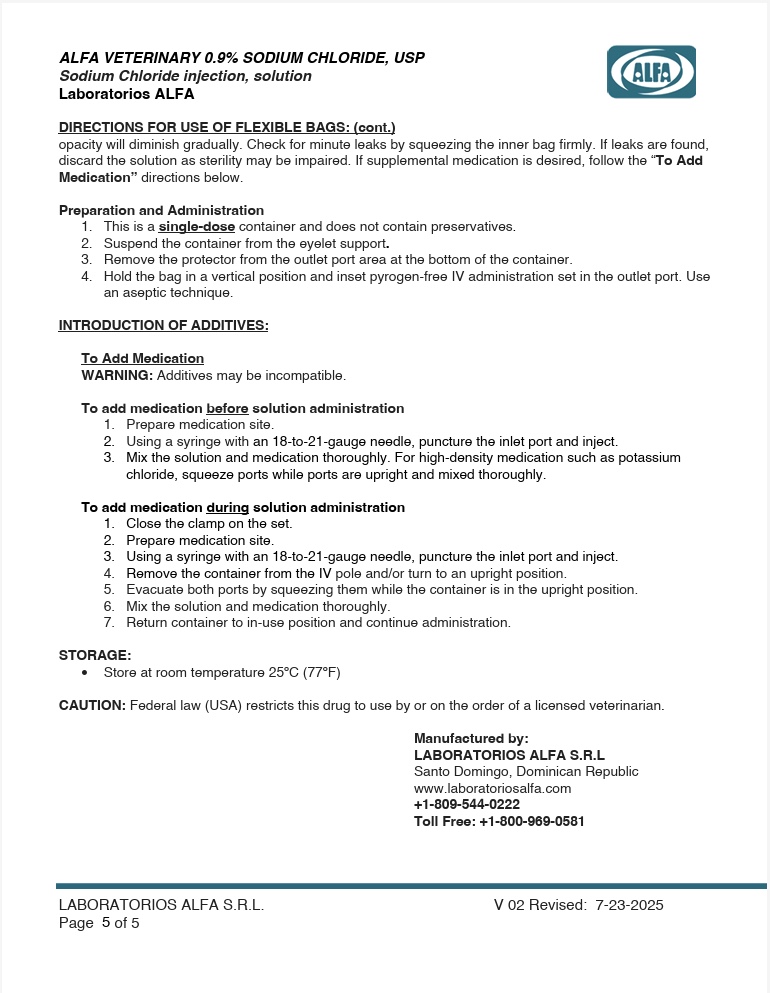 DRUG LABEL: Alfa Veterinary 0.9% Sodium Chloride
NDC: 72483-203 | Form: INJECTION, SOLUTION
Manufacturer: Laboratorios Alfa SRL
Category: animal | Type: PRESCRIPTION ANIMAL DRUG LABEL
Date: 20250814

ACTIVE INGREDIENTS: SODIUM CHLORIDE 900 mg/100 mL
INACTIVE INGREDIENTS: Water

DESCRIPTION

Veterinary 0.9% Sodium Chloride solution is sterile and non-pyrogenic. It is a parenteral solution in a single-dose container containing sodium chloride in water for injection intended for intravenous administration. Discard the unused portion. Does not contain antimicrobial agents. Composition, osmolarity, pH, and caloric content are shown in Table 1.

Table 1: Veterinary 0.9% Sodium Chloride Injection, USP
Size (mL) | Composition (mg/100 mL) | Osmolarity; (mOsmol/L); (Calculated) | pH | Concentration; (mEq/L) |  | Caloric; Content; (kcal/L)
Size (mL) | Sodium Chloride, USP; (NaCl) | Osmolarity; (mOsmol/L); (Calculated) | pH | Sodium | Chloride | Caloric; Content; (kcal/L)
BOTTLES
100 | 900 | 308 | 4.5-7.0 | 154 | 154 | 0
250 | 900 | 308 | 4.5-7.0 | 154 | 154 | 0
500 | 900 | 308 | 4.5-7.0 | 154 | 154 | 0
1000 | 900 | 308 | 4.5-7.0 | 154 | 154 | 0
BAGS
100 | 900 | 308 | 4.5-7.0 | 154 | 154 | 0
250 | 900 | 308 | 4.5-7.0 | 154 | 154 | 0
500 | 900 | 308 | 4.5-7.0 | 154 | 154 | 0
1000 | 900 | 308 | 4.5-7.0 | 154 | 154 | 0
3000 | 900 | 308 | 4.5-7.0 | 154 | 154 | 0
5000 | 900 | 308 | 4.5-7.0 | 154 | 154 | 0

The plastic container, a semi-rigid bottle, is made of a low-density polyethylene which is a flexible and resistant material that provides an excellent compatibility with a maximum number of pharmaceuticals, reducing the risk of interactions. No venting is necessary during infusion.

The flexible bag is made from polyvinyl chloride (PVC), which is a flexible and resistant material that provides an excellent compatibility with a maximum number of pharmaceuticals, reducing the risk of interactions. No venting is necessary during infusion.

OTHER SAFETY INFORMATION

CAUTION: Federal law (USA) restricts this drug to use by or on the order of a licensed veterinarian.

CLINICAL PHARMACOLOGY

Veterinary 0.9% Sodium Chloride Injection, USP solution has value as a source of water and electrolytes. It may induce diuresis depending on the clinical condition of the patient.

Sodium, the major cation of the extracellular fluid, functions primarily in the control of water distribution, fluid balance, and osmotic pressure of body fluids. Sodium is also associated with chloride and bicarbonate in the regulation of the acid-base equilibrium of body fluid.

Chloride, the major extracellular anion, closely follows the metabolism of sodium, and changes in the acid-base balance of the body are reflected by changes in the chloride concentration.

INDICATIONS AND USAGE

Veterinary 0.9% Sodium Chloride Injection, USP solution is indicated for parenteral replenishment of fluid and sodium chloride as required by the clinical condition of the patient. Used as a source of electrolytes and water for hydration.

CONTRAINDICATIONS

• These solutions are contraindicated where the administration of sodium or chloride could be clinically detrimental.

WARNINGS

- Veterinary 0.9% Sodium Chloride Injection, USP should not be administered simultaneously with blood through the same administration set because of the possibility of pseudo agglutination or hemolysis
- Solutions containing sodium ions should be used with great care, if at all, in patients with congestive heart failure, severe renal insufficiency, and in clinical states in which there is sodium retention with edema. In patients with diminished renal function, administration of solutions containing sodium ions may result in sodium retention.
- In patients with diminished renal function, administration of the solution may result in sodium retention proportional to the electrolyte concentrations of the injections.
- Infusion of isotonic (0.9%) sodium chloride during or immediately after surgery may result in excessive sodium retention. Use the patient’s circulatory system status as a guide.
- The intravenous administration of Veterinary 0.9% Sodium Chloride solution can cause fluid and/or solute overloading resulting in dilution of serum electrolyte concentrations, overhydration, congested states, or pulmonary edema
- The risk of dilutive states is inversely proportional to the electrolyte concentrations of the injections
- The risk of solute overload causing congested states with peripheral and pulmonary edema is directly proportional to the electrolyte concentrations of the injections

The container label for these injections bears the statement:

- Do not administer simultaneously with blood
- Keep out of the reach of children

PRECAUTIONS

- These solutions should be used with care in patients with hypervolemia, renal insufficiency, urinary tract obstruction, or impending or frank cardiac decompensation.
- Extraordinary electrolyte losses such as may occur during protracted nasogastric suction, vomiting, diarrhea or gastrointestinal fistula drainage may necessitate additional electrolyte supplementation.
- Additional essential electrolytes, minerals, and vitamins should be supplied as needed.
- Sodium-containing solutions should be administered with caution to patients receiving corticosteroids or corticotropin, or to other salt-retaining patients. Care should be exercised in administering solutions containing sodium to patients with renal or cardiovascular insufficiency, with or without congestive heart failure, particularly if they are postoperative or elderly.
- Infusion of more than one liter of isotonic (0.9%) sodium chloride per day may supply more sodium and chloride than normally found in serum, and can exceed normal tolerance, resulting in hypernatremia; this may also cause a loss of bicarbonate ions, resulting in an acidifying effect.
- To minimize the risk of possible incompatibilities arising from mixing any of these solutions with other additives that may be prescribed, the final infusate should be inspected for cloudiness or precipitation immediately after mixing, prior to administration, and periodically during administration.
- Do not connect the plastic containers in series in order to avoid air embolism.
- If the administration is controlled by a pumping device, care must be taken to discontinue pumping action before the container runs dry or air embolism may result. These solutions are intended for intravenous administration using sterile equipment. It is recommended that the intravenous administration apparatus be replaced at least once every 24 hours.
- This is a hypotonic solution and as such should not be used for resuscitation
- Do not administer unless the solution is clear, and both seal and container are intact

ADVERSE REACTIONS

• Reactions which may occur because of the injection, or the technique of administration include febrile response, infection at the site of injection, venous thrombosis or phlebitis extending from the site of injection, extravasation, and hypervolemia
• If an adverse reaction does occur, discontinue the infusion, evaluate the patient, institute appropriate therapeutic countermeasures, and save the remainder of the fluid for examination if deemed necessary

OVERDOSAGE

In the event of over-hydration or solute overload, re-evaluate the patient and institute appropriate corrective measures. See Warnings, Precautions, and Adverse Reactions.

DOSAGE AND ADMINISTRATION

- Do not administer unless a solution is clear, and the seal is intact
- As directed by a veterinarian. Dosage is dependent upon the age, weight, and clinical condition of the patient as well as laboratory determinations
- Parenteral drug products should be inspected visually for particulate matter and discoloration prior to administration whenever solution and container permit
- All injections in plastic containers are intended for intravenous administration using sterile equipment
- This product should be warmed to body temperature and administered slowly
- Additives may be incompatible. Complete information is not available. Those additives known to be incompatible should not be used. Consult with a veterinarian, if available.
- If, in the informed judgment of the veterinarian, it is deemed advisable to introduce additives, use an aseptic technique. Mix thoroughly when additives have been introduced.
- Do not store any unused portion of the solution containing additives. Discard unused portion.

DIRECTIONS FOR USE OF PLASTIC BOTTLE:
To Open:
Remove the overwrap seal over the bottle cap. Visually inspect the container for leaks. If leaks or the seal is torn, broken, or missing, discard the solution as sterility may be impaired. Use the solution immediately after the bottle is opened. Discard unused portion. If supplemental medication is desired, follow the “To Add Medication” directions below.

Preparation and Administration
1. This is a single-dose container and does not contain preservatives.
2. Suspend the container from the eyelet support.
3. Remove the plastic protector from the outlet port area at the bottom of the container.
4. Hold the bottle in a vertical position and inset pyrogen-free IV administration set in the outlet port. Use aseptic Technique.

DIRECTIONS FOR USE OF FLEXIBLE BAGS:
To Open:
Remove the overwrap downside at the slit and remove the solution container. Visually inspect the container. If the outlet port protector is damaged, detached, or not present, discard the container as solution path sterility may be impaired. Some opacity of the plastic due to moisture absorption during the sterilization process may be observed. This is normal and does not affect the solution quality or safety. The opacity will diminish gradually. Check for minute leaks by squeezing the inner bag firmly. If leaks are found, discard the solution as sterility may be impaired. If supplemental medication is desired, follow the “To Add Medication” directions below.

Preparation and Administration
1. This is a single-dose container and does not contain preservatives.
2. Suspend the container from the eyelet support.
3. Remove the protector from the outlet port area at the bottom of the container.
4. Hold the bag in a vertical position and inset pyrogen-free IV administration set in the outlet port. Use an aseptic technique.

INTRODUCTION OF ADDITIVES:

To Add Medication
WARNING: Additives may be incompatible.

To add medication before solution administration
1. Prepare medication site.
2. Using a syringe with an 18-to-22 gauge needle, puncture the inlet port and inject.
3. Mix the solution and medication thoroughly. For high-density medication such as potassium chloride, squeeze ports while ports are upright and mixed thoroughly.

To add medication during solution administration
1. Close the clamp on the set.
2. Prepare medication site.
3. Using a syringe with an 18-to-22 gauge needle, puncture the inlet port and inject.
4. Remove the container from the IV pole and/or turn to an upright position.
5. Evacuate both ports by squeezing them while the container is in the upright position.
6. Mix the solution and medication thoroughly.
7. Return container to in-use position and continue administration.

HOW SUPPLIED

Veterinary 0.9% Sodium Chloride, USP (Injectable) solution is available in the following sizes:

BOTTLES | NDC#
VET 0.9% Sodium Chloride, 1000 mL | 72483-203-10
VET 0.9% Sodium Chloride, 500 mL | 72483-203-05
VET 0.9% Sodium Chloride, 250 mL | 72483-203-25
VET 0.9% Sodium Chloride, 100 mL | 72483-203-01
BAGS | NDC#
VET 0.9% Sodium Chloride, 5000 mL | 72483-203-02
VET 0.9% Sodium Chloride, 3000 mL | 72483-203-03
VET 0.9% Sodium Chloride, 1000 mL | 72483-203-04
VET 0.9% Sodium Chloride, 500 mL | 72483-203-06
VET 0.9% Sodium Chloride, 250 mL | 72483-203-07
VET 0.9% Sodium Chloride, 100 mL | 72483-203-08

STORAGE

- Store at room temperature 25ºC (77ºF)

PACKAGE INSERT

For Animal Use Only

0.9% Sodium Chloride injection (BOTTLES)

0.9% SODIUM CHLORIDE Injection, USP

For Veterinary Use Only

NDC: 72483-203-10 1000 mL 0.9% Sodium Chloride
NDC: 72483-203-05 500 mL 5% 0.9% Sodium Chloride
NDC: 72483-203-25 250 mL 5% 0.9% Sodium Chloride
NDC: 72483-203-01 100 mL 5% 0.9% Sodium Chloride

0.9% Sodium Chloride injection (BAGS)

0.9% SODIUM CHLORIDE Injection, USP

For Veterinary Use Only

NDC: 72483-203-02 5000 mL0.9% Sodium Chloride

NDC: 72483-203-03 3000 mL 0.9% Sodium Chloride

NDC: 72483-203-04 1000 mL 0.9% Sodium Chloride

NDC: 72483-203-06 500 mL 5% 0.9% Sodium Chloride

NDC: 72483-203-07 250 mL 5% 0.9% Sodium Chloride

NDC: 72483-203-08 100 mL 5% 0.9% Sodium Chloride